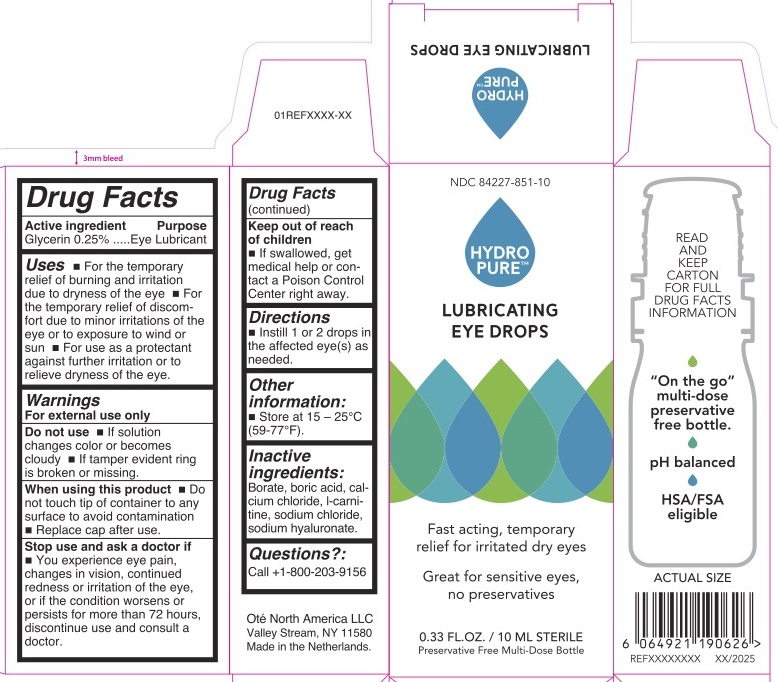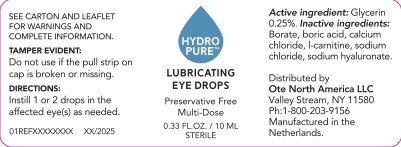 DRUG LABEL: Hydropure Lubricating Eye Drops
NDC: 84227-851 | Form: SOLUTION/ DROPS
Manufacturer: OTE North America
Category: otc | Type: HUMAN OTC DRUG LABEL
Date: 20250214

ACTIVE INGREDIENTS: GLYCERIN 2.5 mg/1 mL
INACTIVE INGREDIENTS: BORIC ACID; SODIUM CHLORIDE; LEVOCARNITINE; BORATE ION; HYALURONATE SODIUM; CALCIUM CHLORIDE

Hydropure Lubricating Eye Drops

Active ingredient

Glycerin 0.25%

Purpose

Eye Lubricant

Uses

■ For the temporary relief of burning and irritation due to dryness of the eye ■ For the temporary relief of discomfort due to minor irritations of the eye or to exposure to wind or sun ■ For use as a protectant against further irritation or to temporarily relieve dryness of the eye

Warnings for External use only.

Keep out of reach of children ■ If swallowed, get medical help or contact a Poison Control Center right away

Do not use ■ If solution changes color or becomes cloudy ■ If tamper evident ring is broken or missing.

When using this product ■ Do not touch tip of container to any surface to avoid contamination

■ Replace cap after use.

Stop use and ask a doctor if

■ You experience eye pain, changes in vision, continued redness or irritation of the eye, or if the condition worsens or persists for more than 72 hours, discontinue use and consult a doctor.

Directions

■ Instill 1 or 2 drops in the affected eye(s) as needed.

INACTIVE INGREDIENT

Inactive ingredients: borate, boric acid, sodium chloride, calcium chloride, l-carnitine, sodium hyaluronate

Other information

■ Store at 15 - 25 C (59-77 F).

Questions?

Call + 1-800-203-9156